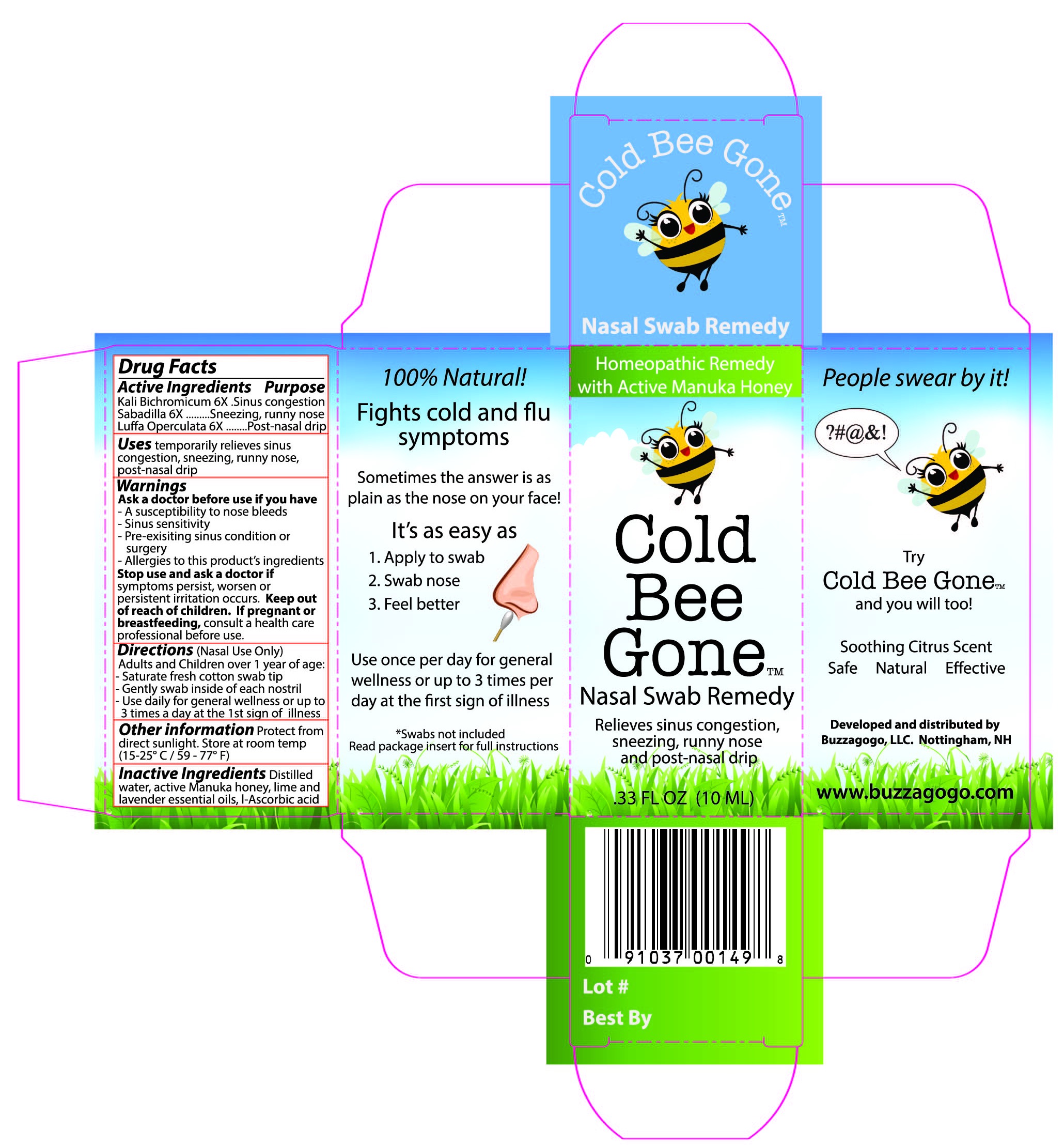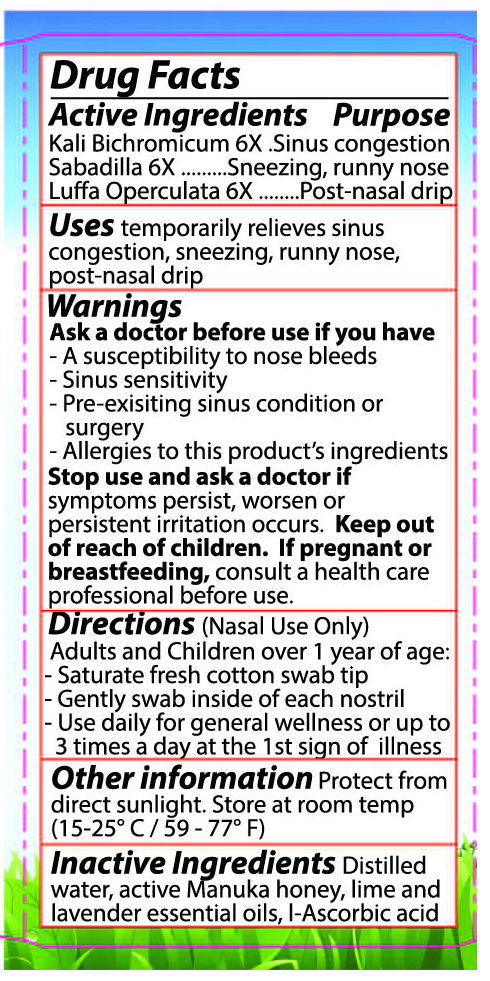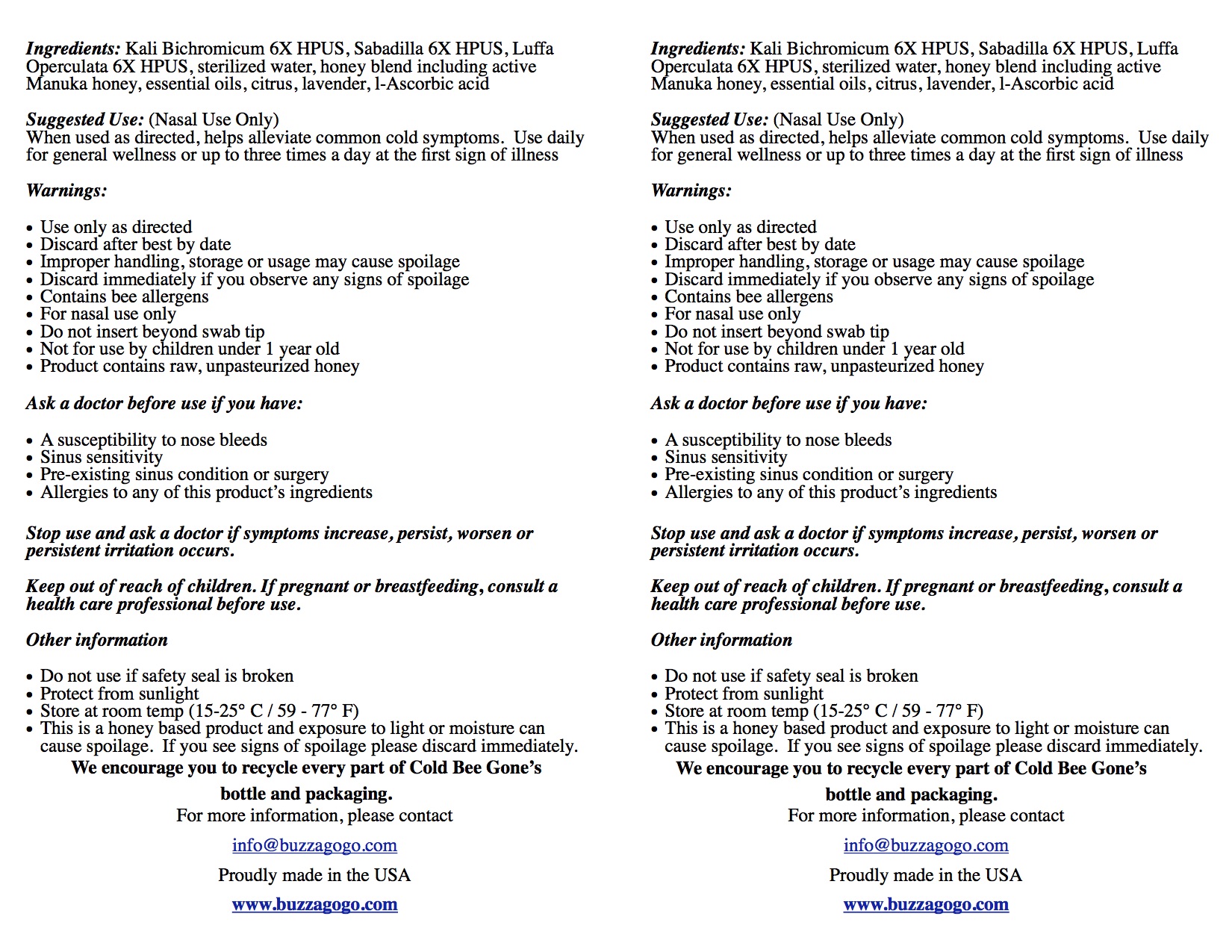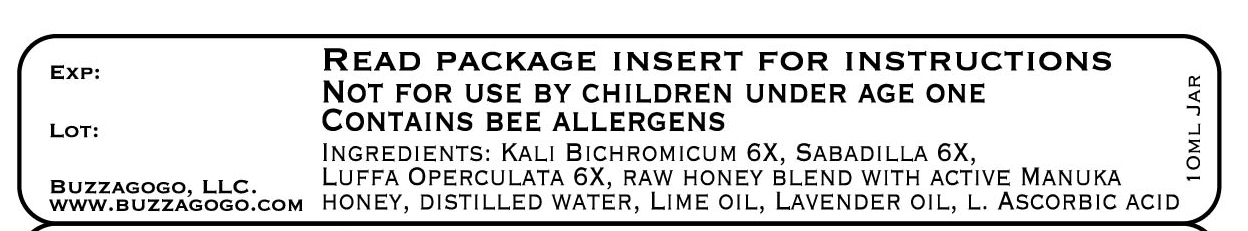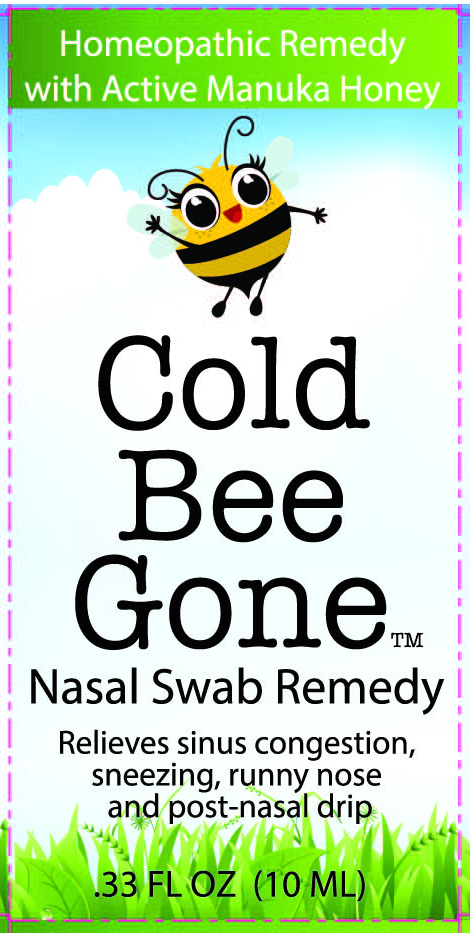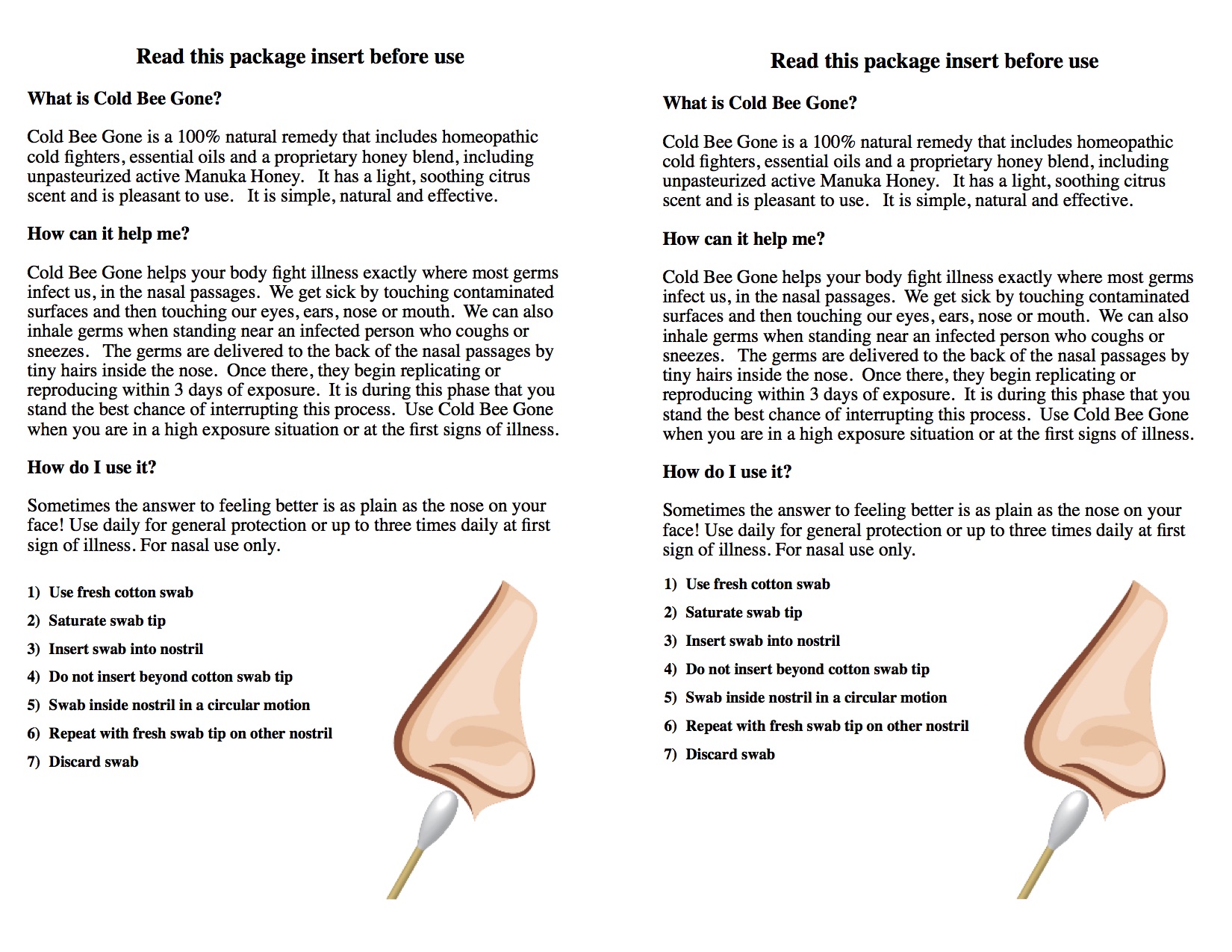 DRUG LABEL: Allergy Bee Gone For Kids
NDC: 70449-1004 | Form: LIQUID
Manufacturer: Buzzagogo, Inc
Category: homeopathic | Type: HUMAN OTC DRUG LABEL
Date: 20221107

ACTIVE INGREDIENTS: POTASSIUM DICHROMATE 6 [hp_X]/1 mL; SCHOENOCAULON OFFICINALE SEED 6 [hp_X]/1 mL; LUFFA OPERCULATA FRUIT 6 [hp_X]/1 mL; GALPHIMIA GLAUCA FLOWERING TOP 6 [hp_X]/1 mL; HISTAMINE DIHYDROCHLORIDE 6 [hp_X]/1 mL
INACTIVE INGREDIENTS: LAVENDER OIL; LIME OIL; WATER; ASCORBIC ACID; HONEY

Allergy Bee Gone For Kids

ACTIVE INGREDIENT

Kali Bichromicum 6X...Sinus congestion

Sabadilla 6X...Sneezing, runny nose

Luffa Operculata 6X...Post-nasal drip